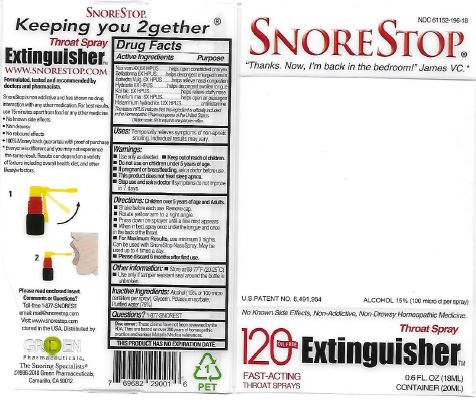 DRUG LABEL: Snore Stop Extinguisher Throat
NDC: 61152-196 | Form: SPRAY
Manufacturer: Green Pharmaceuticals Inc
Category: homeopathic | Type: HUMAN OTC DRUG LABEL
Date: 20240108

ACTIVE INGREDIENTS: ATROPA BELLADONNA 6 [hp_X]/4.5 mL; EPHEDRA DISTACHYA FLOWERING TWIG 6 [hp_X]/4.5 mL; HISTAMINE DIHYDROCHLORIDE 12 [hp_X]/4.5 mL; GOLDENSEAL 6 [hp_X]/4.5 mL; POTASSIUM DICHROMATE 6 [hp_X]/4.5 mL; STRYCHNOS NUX-VOMICA SEED 6 [hp_X]/4.5 mL; TEUCRIUM MARUM 6 [hp_X]/4.5 mL
INACTIVE INGREDIENTS: ALCOHOL; GLYCERIN; POTASSIUM SORBATE; WATER

SnoreStop 120 Fast Acting Extinguisher Throat

Ingredients (HPUS):

Belladonna 6x, Ephedra vulg. 6x, Histaminium hydrochloricum 12x, Hydrastis 6x, Kali bic 6x, Nux vom. 4x, 6x, Teucrium mar. 6x.

Inactive Ingredients:

Alcohol (100 micro centiliters per spray), Glycerin, Potassium sorbate, Purified water (75%).

Uses:

Temporarily relieves symptoms of non-apneic snoring. Individual results may vary.

Warnings:

Use only as directed. Keep out of reach of children. Do not use on children under 5 years of age. If pregnant or breastfeeding, ask a doctor before use. This product does not treat sleep apnea. Stop use and ask a doctor if symptoms do not improve in 7 days.

Keep out of reach of children.

Directions:

Children over 5 years of age and Adults.

- Shake before each use. Remove cap.
- Rotate yellow arm to a right angle.
- Press down on sprayer until a fine mist appears.
- When in bed, spray spray once under the tongue and once in the back of the throat.
- For Maximum Results, use minimum 3 nights.

Can be used with SnoreStop NasoSpray. May be used up to 4 times a day.

- Please discard 6 months after first use.

Purpose:

Temporarily helps stop or reduce symptoms of non-apneic snoring. Individual results may vary.

Other information

- Store at 68-77°F (20-25°C)
- Use only if tamper resistant seal around the bottle is unbroken.

Questions?

1-877-SNOREST

Snore Stop Extinguisher Throat Spray